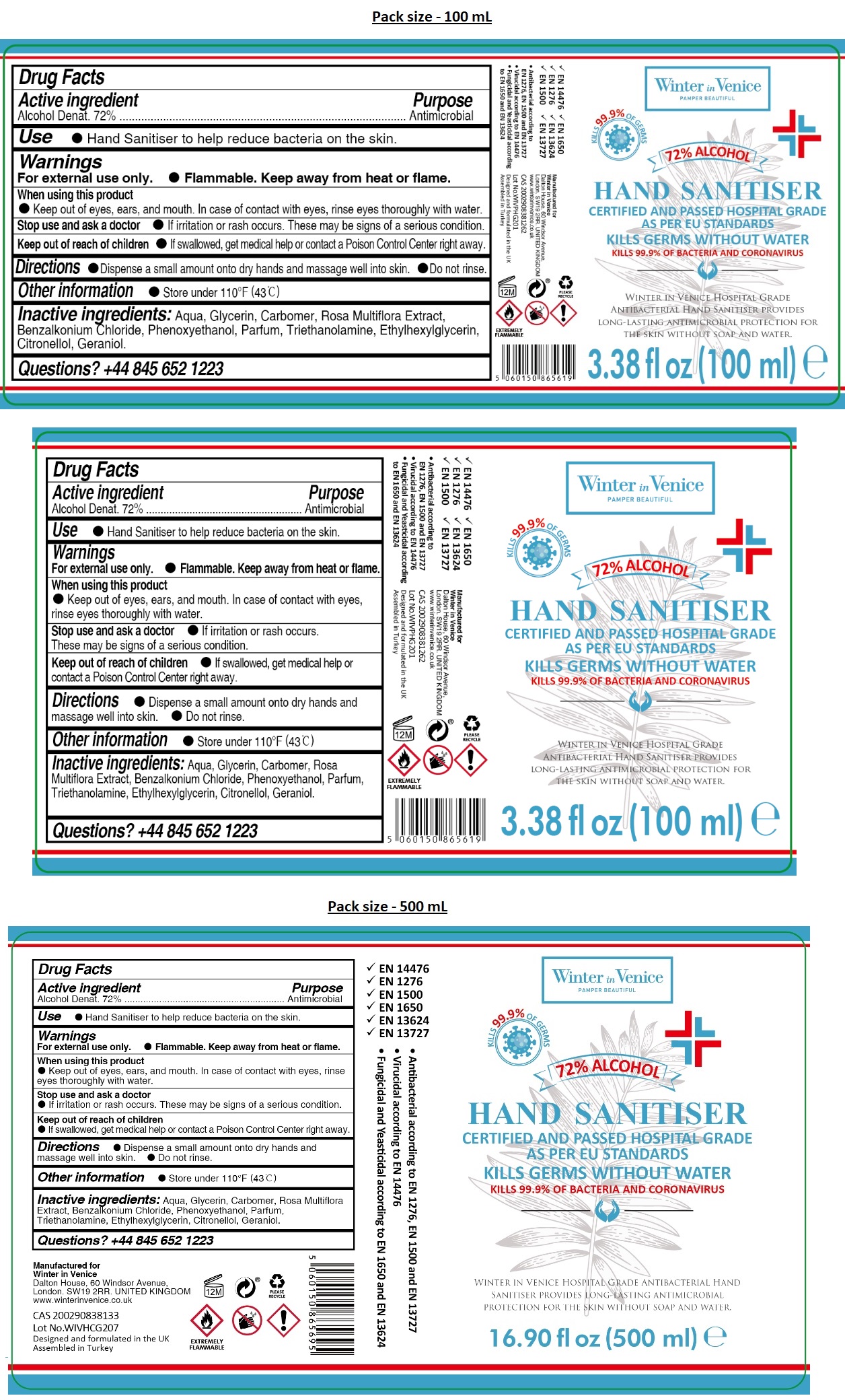 DRUG LABEL: Winter in Venice Hospital Grade Hand Sanitizer
NDC: 78609-124 | Form: GEL
Manufacturer: WIV Global Limited
Category: otc | Type: HUMAN OTC DRUG LABEL
Date: 20201005

ACTIVE INGREDIENTS: ALCOHOL 72 mL/100 mL
INACTIVE INGREDIENTS: WATER; GLYCERIN; CARBOMER HOMOPOLYMER, UNSPECIFIED TYPE; ROSA MULTIFLORA WHOLE; BENZALKONIUM CHLORIDE; PHENOXYETHANOL; TROLAMINE; ETHYLHEXYLGLYCERIN; .BETA.-CITRONELLOL, (R)-; GERANIOL

Winter in Venice HAND SANITISER

Active ingredient

Alcohol Denat. 72%

Purpose

Antimicrobial

INDICATIONS AND USAGE

Use • Hand Sanitiser to help reduce bacteria on the skin.

Warnings

For external use only. • Flammable. Keep away from heat or flame.

When using this product

• Keep out of eyes, ears, and mouth. In case of contact with eyes, rinse eyes thoroughly with water.

Stop use and ask a doctor

• if irritation or rash occurs. These may be signs of a serious condition.

Keep out of reach of children

• If swallowed, get medical help or contact a Poison Control Center right away.

DOSAGE AND ADMINISTRATION

Directions • Dispense a small amount onto dry hands and massage well into skin. • Do not rinse.

Other information • Store under 110°F (43°C)

INACTIVE INGREDIENT

Inactive ingredients: Aqua, Glycerin, Carbomer, Rosa Multiflora Extract, Benzalkonium Chloride, Phenoxyethanol, Parfum, Triethanolamine, Ethylhexylglycerin, Citronellol, Geraniol.

Questions? +44 845 652 1223

KILLS 99.9% OF GERMS

CERTIFIED AND PASSED HOSPITAL GRADE AS PER EU STANDARDS

KILLS GERMS WITHOUT WATER

KILLS 99.9% OF BACTERIA AND CORONAVIRUS

WINTER IN VENICE HOSPITAL GRADE ANTIBACTERIAL HAND SANITISER PROVIDES LONG-LASTING ANTIMICROBIAL PROTECTION FOR THE SKIN WITHOUT SOAP AND WATER.

- EN 14476
- EN 1276
- EN 1500
- EN 1650
- EN 13624
- EN 13727

• Antibacterial according to EN 1276, EN 1500 and EN 13727

• Virucidal according to EN 14476

• Fungicidal and Yeasticidal according to EN 1650 and EN 13624

Manufactured for

Winter in Venice

Dalton House, 60 Windsor Avenue,

London. SW19 2RR. UNITED KINGDOM

www.winterinvenice.co.uk

Designed and formulated in the UK

Assembled in Turkey